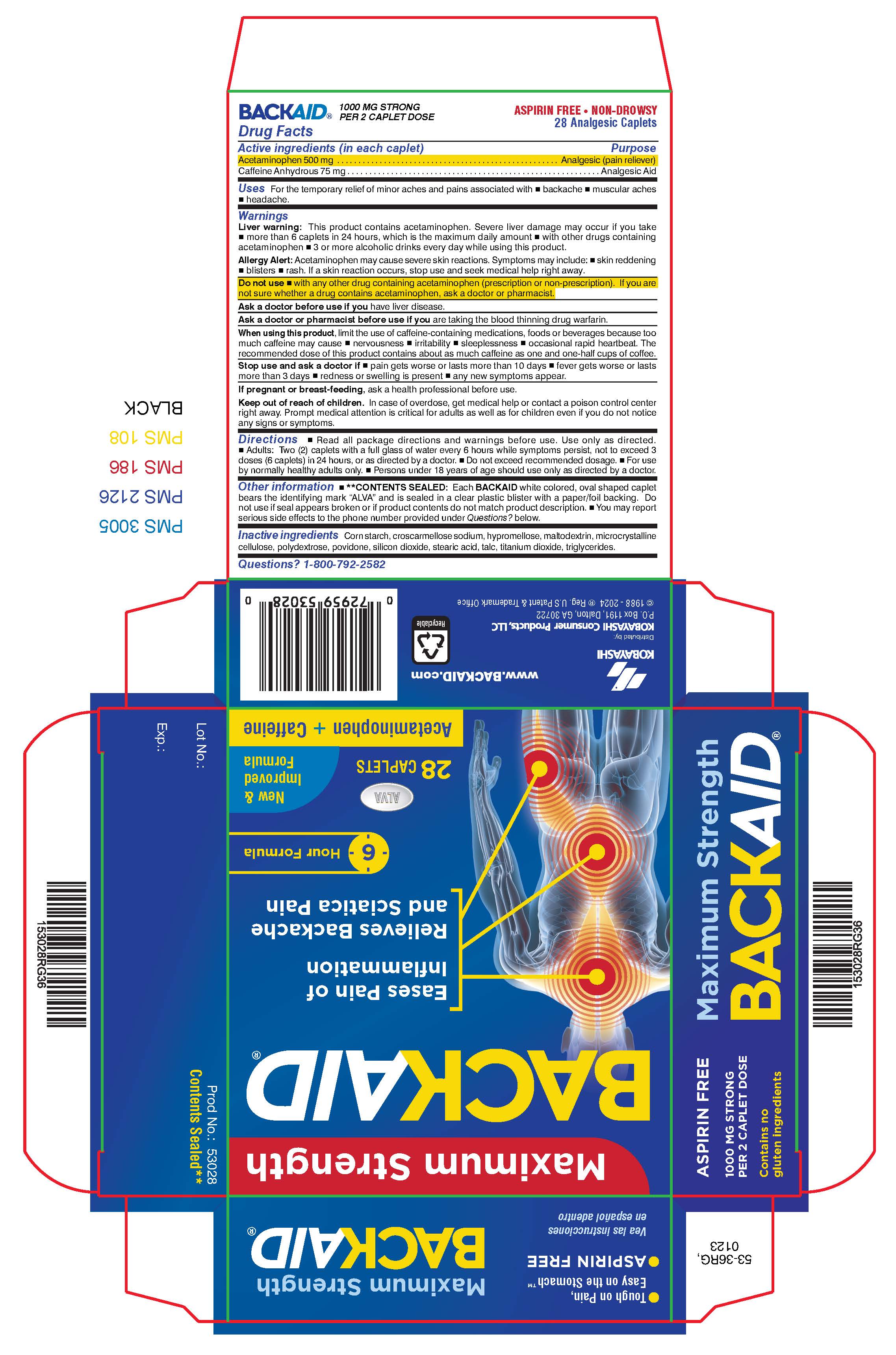 DRUG LABEL: BackAid
NDC: 52389-253 | Form: TABLET, FILM COATED
Manufacturer: Kobayashi Healthcare International, Inc.
Category: otc | Type: HUMAN OTC DRUG LABEL
Date: 20251021

ACTIVE INGREDIENTS: CAFFEINE 75 mg/1 1; ACETAMINOPHEN 500 mg/1 1
INACTIVE INGREDIENTS: MALTODEXTRIN; STARCH, CORN; CROSCARMELLOSE SODIUM; HYPROMELLOSES; TALC; CELLULOSE, MICROCRYSTALLINE; POLYDEXTROSE; SILICON DIOXIDE; C10-18 TRIGLYCERIDES; STEARIC ACID; TITANIUM DIOXIDE; POVIDONE

BackAid caffeine

Active ingredients (in each caplet)

Acetaminophen, 500 mg

Caffeine, 75 mg

Purpose

Analgesic (pain reliever)

Analgesic aid

Uses

For the temporary relief of minor aches and pains associated with

- backache
- muscular aches
- headache

Warnings

Liver Warning: This product contains acetaminophen. Severe liver damage may occur if you take

- more than 6 caplets in 24 hours, which is the maximum daily amount
- with other drugs containing acetaminophen
- 3 or more alcoholic drinks every day while using this product.

Allergy Alert: Acetaminophen may cause severe skin reactions. Symptoms may include:

- skin reddening
- blisters
- rash

If a skin reaction occurs, stop use and seek medical help right away.

Do not use

- with any other drug containing acetaminophen (prescription or non-prescription). If you are not sure whether a drug contains acetaminophen, ask a doctor or pharmacist.

Ask a doctor before use if you have liver disease.

Ask a doctor or pharmacist before use if you are taking the blood thinning drug warfarin.

When using this product, limit the use of caffeine-containing medications, foods or beverages because too mush caffeine may cause

- nervousness
- irritability
- sleeplessness
- occasional rapid heartbeat

The recommended dose of this product contains about as much caffeine as one and one-half cups of coffee.

Stop use and ask a doctor if

- pain gets worse or lasts more than 10 days
- fever gets worse or lasts more than 3 days
- redness or swelling is present
- any new symptoms appear

PREGNANCY OR BREAST FEEDING

If pregnant or breast-feeding, ask a health professional before use.

Keep out of reach of children. In case of overdose, get medical help or contact a poison control center right away. Prompt medical attention is critical for adults as well as for children even if you do not notice any signs or symptoms.

Directions

- Read all package directions and warnings before use. Use only as directed.
- Adults: Two (2) caplets with a full glass of water every 6 hours while symptoms persist, not to exceed 3 doses (6 caplets) in 24 hours, or as directed by a doctor.
- Do not exceed recommended dosage.
- For use by normally healthy adults only.
- Persons under 18 years of age should use only as directed by a doctor.

Other information

**CONTENTS SEALED: Each BACKAID white colored, oval shaped caplet bears the identifying mark "ALVA" and is sealed in a clear plastic blister with a paper/foil backing. Do not use if seal appears broken or if product contents do not match product description.

- You may report serious side effects to the phone number provided under Questions? below.

Inactive ingredients

Corn starch, croscarmellose sodium, hypromellose, maltodextrin, microcrystalline cellulose, polydextrose, povidone, silicon dioxide, stearic acid, talc, titanium dioxide, triglycerides.

Questions?

1-800-792-2582.

Package insert

New & Improved Formula

Maximum Strength

BACKAID

6 Hour Formula

Acetaminophen + Caffeine

- Eases Pain of Inflammation
- Relieves Backache and Sciatica Pain

Active ingredients: Each caplet contains: acetaminophen 500 mg (analgesic/pain reliever) and caffeine anhydrous 75 mg (analgesic aid).

Uses: For the temporary relief of minor aches and pains associated with • backache • muscular aches • headache

Warnings

Liver Warning: This product contains acetaminophen. Severe liver damage may occur if you take • more than 6 caplets in 24 hours, which is the maximum dally amount • with other drugs containing acetaminophen • 3 or more alcoholic drinks every day while using this product.

Allergy Alert: Acetaminophen may cause severe skin reactions. Symptoms may include • skin reddening • blisters • rash. If a skin reaction occurs, stop use and seek medical help right away.

Do not use • with any other drug containing acetaminophen (prescription or non-prescription). If you are not sure whether a drug contains acetaminophen, ask a doctor or pharmacist.

Ask a doctor before use if you have liver disease.

Ask a doctor or pharmacist before use if you are taking the blood thinning drug warfarin.

When using this product, limit the use of caffeine-containing medications, foods or beverages because too much cafeine may cause

- nervousness
- irritability
- sleeplessness
- occassional rapid heatbeat

The recommended dose of this product contains about as much caffeine as one and one-half cups of coffee.

Stop use and ask a doctor if

- pain gets worse or lasts more than 10 days
- fever gets worse or lasts more than 3 days
- redness or welling is present
- any new symptoms appear

If pregnant or breast feeding, ask a health professional before use.

Keep out of reach of children. In case of overdose, get medical help or contact a poison control center right away. Prompt medical attention is critical for adults as well as for children even if you do not notice any signs or symptoms.

Directions:

- Read all package directions and warnings before use. Use only as directed.
- Adults: Two (2) caplets with a full glass of water every 6 hours while symptoms persist, not to exceed 3 doses (6 caplets) in 24 hours, or as directed by a doctor.
- Do not exceed recommended dosage.
- For use by normally healthy adults only.
- Persons under 18 years of age should use only as directed by a doctor.

Other information:

**CONTENTS SEALED: Each BACKAID white colored, oval shaped caplet bears the identifying mark "ALVA" and is sealed in a clear plastic blister with a paper/foil backing or in a bottle with a safety seal under the cap. Do not use if seal appears broken or if product contents do not match product description. • You may report serious side effects to the phone number provided under Questions? below.

Inactive ingredients Corn starch, croscarmellose sodium, hypromellose, maltodextrin, microcrystalline cellulose, polydextrose, povidone, silicon dioxide, stearic acid, talc, titanium dioxide, triglycerides.

Questions? 1-800-792-2582

Fórmula nueva y mejorada

Maxima concentración

BACKAID

Fórmula de 6 horas

Acetaminofeno + cafeina

- Alivia el dolor de la inflamación
- Alivia el dolor de espalda y el dolor ciático

Ingredientes activos: Cada comprimido oblongo contiene: 500 mg de acetaminofeno (un analgésico, alivia el dolor) y 75 mg de cafeína anhidra (ayuda analgésica).

Usos: Para el alivio temporal de dolores menores asociados con

- dolor de espalda
- dolores musculares
- dolor de cabeza

Advertencias:

Advertencia hepática: Este producto contiene acetaminofeno. Puede producirse un daño hepático grave si usted toma:

- más de 6 comprimidos oblongos en 24 horas, que es la cantidad diaria máxima
- otros fármacos que contienen acetaminofeno al mismo tiempo
- 3 o más bebidas alcohólicas cada día mientras usa este producto.

Alerta de alergias: El acetaminofeno puede causar reacciones graves en la piel. Los síntomas pueden incluir:

- enrojecimiento de la piel
- ampollas
- sarpullido

Si se produce una reacción en la piel, deje de usar el producto y busque ayuda médica de inmediato.

No lo use

- con ningún otro fármaco que contenga acetaminofeno (de venta con receta o sin ella). Si no está seguro respecto de si un fármaco contiene acetaminofeno o no, pregúntele a un médico o farmacéutico.

Pregúntele a un médico antes de usarlo si tiene enfermedad hepática.

Pregúntele a un médico o farmacéutico antes de usarlo si está tomando el fármaco anticoagulante warfarina.

Cuando use este producto, limite el uso de medicamentos, alimentos o bebidas que contengan cafeína ya que demasiada cafeína puede provocar:

- nerviosismo
- irritabilidad
- insomnio
- latidos cardíacos rápidos ocasionales

La dosis recomendada de este producto contiene aproximadamente la misma cantidad de cafeína que una taza y media de café.

Deje de usarlo y consulte a un médico si

- el dolor empeora o dura más de 10 días
- la fiebre empeora o dura más de 3 días
- aparece enrojecimiento o hinchazón
- se presentan síntomas nuevos.

Si está embarazada o está amamantando, consulte a un profesional de la salud antes de usarlo.

Manténgalo fuera del alcance de los niños. En caso de sobredosis, obtenga ayuda médica o comuníquese de inmediato con un centro de toxicología. La atención médica inmediata es fundamental tanto para los adultos como para los niños, incluso si no observa signos ni síntomas.

Indicaciones:

- Lea todas las indicaciones y advertencias del envase antes de usarlo. Usar según indicaciones.
- Adultos: Dos (2) comprimidos oblongos con un vaso lleno de agua cada 6 horas mientras los síntomas persisten, sin exceder las 3 dosis (6 comprimidos oblongos) en 24 horas, o según lo indique un médico.
- No exceda la dosificación recomendada.
- Para uso por parte de adultos normalmente sanos únicamente.
- Las personas menores de 18 años deben usarlo solo según las indicaciones de un médico.

Información adicional:

- **CONTENIDO SELLADO: Cada comprimido de BACKAID, de forma ovalada y color blanco, lleva la marca identificatoria “ALVA” y está sellado en un blíster de plástico transparente con un recubrimiento posterior de papel/aluminio, o en un frasco con un sello de seguridad debajo de la tapa. No lo use si el sello parece estar roto o si el contenido del producto no coincide con la descripción del producto.
- Puede informar efectos secundarios graves al número de teléfono que aparece en la sección ¿Tiene preguntas? a continuación.

Ingredientes inactivos: almidón de maíz, croscarmelosa sódica, hipromelosa, maltodextrina, celulosa microcristalina, polidextrosa, povidona, dióxido de silicio, ácido esteárico, talco, dióxido de titanio, triglicéridos.

¿Tiene preguntas? 1-800-792-2582